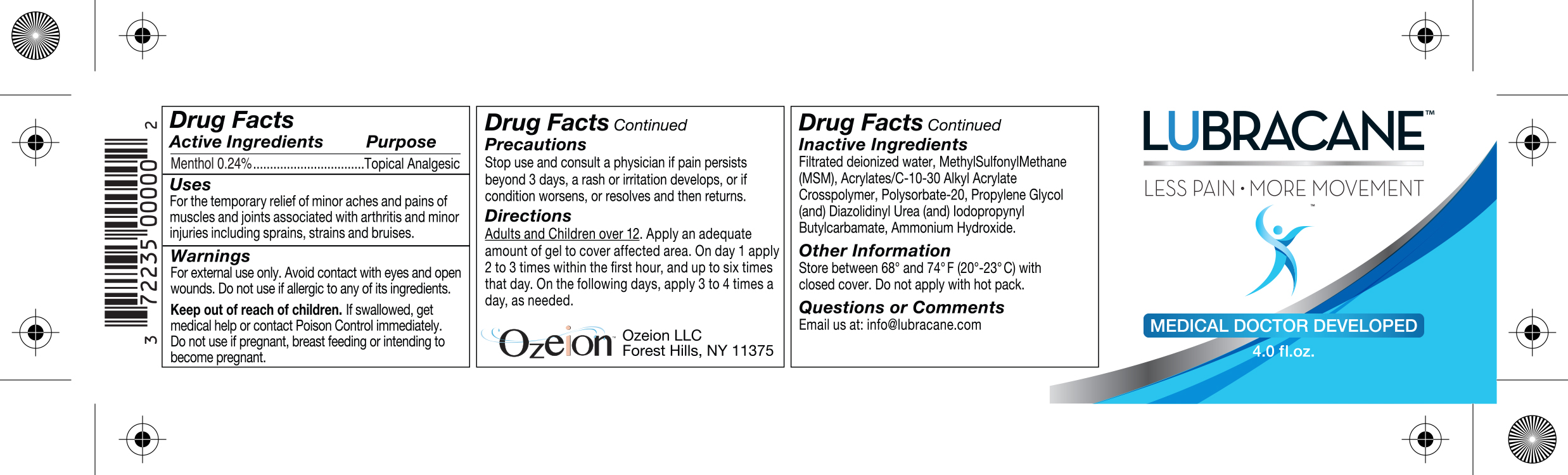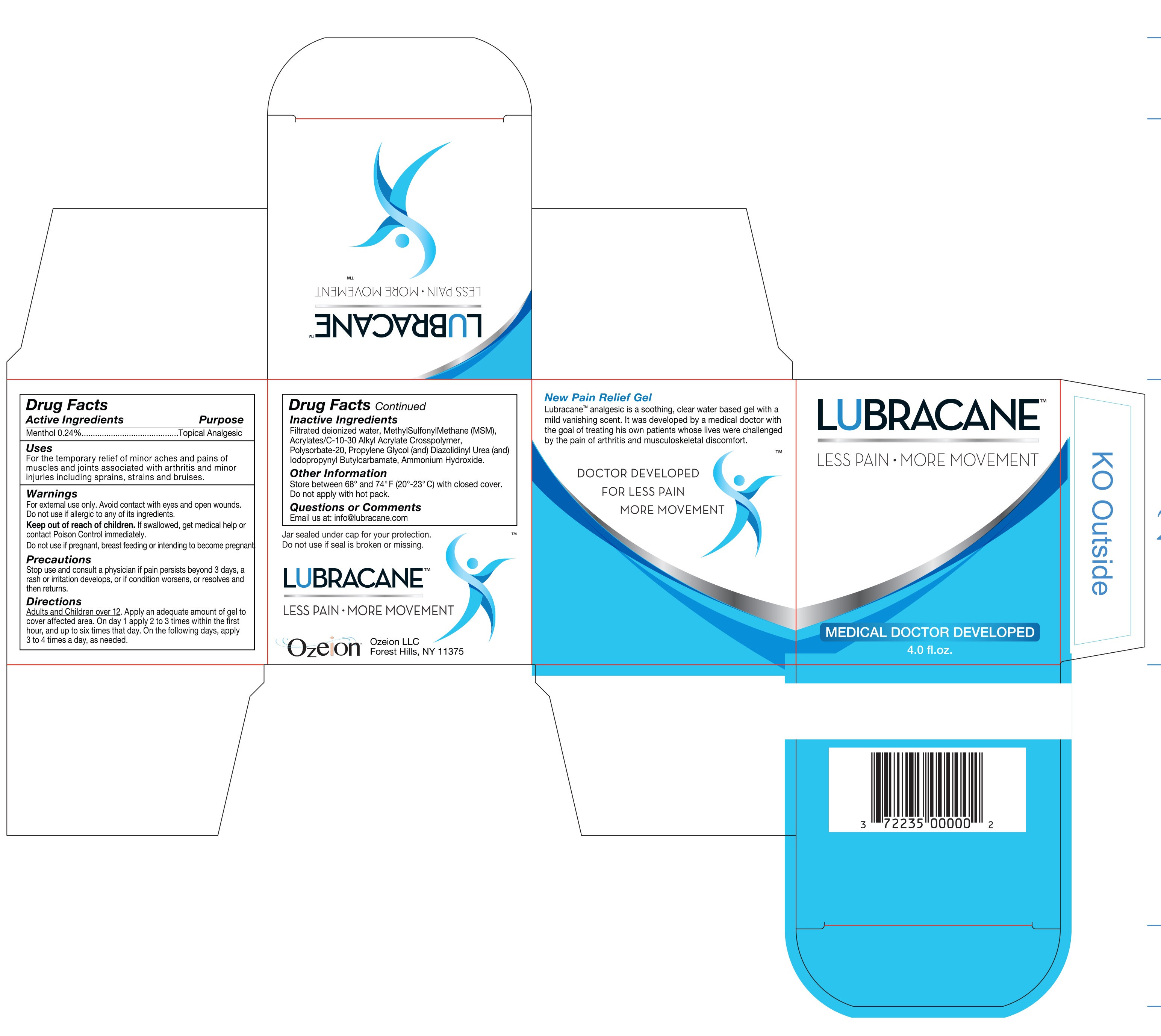 DRUG LABEL: Lubracane
NDC: 72235-5838 | Form: GEL
Manufacturer: Ozeion LLC
Category: otc | Type: HUMAN OTC DRUG LABEL
Date: 20241231

ACTIVE INGREDIENTS: MENTHOL 0.24 mg/1 mL
INACTIVE INGREDIENTS: DIMETHYL SULFONE; CARBOMER INTERPOLYMER TYPE A (ALLYL SUCROSE CROSSLINKED); DIAZOLIDINYL UREA; POLYSORBATE 20; AMMONIA; WATER; PROPYLENE GLYCOL; IODOPROPYNYL BUTYLCARBAMATE

Lubracane

Active Ingredients

Menthol 0.24% Topical Analgesic

INDICATIONS AND USAGE

Uses

For the temporary relief of minor aches and pains of muscles and joints associated with arthritis and minor injuries including sprains, strains and bruises.

WARNINGS

Warnings

For external use only. Avoid contact with eyes and open wounds. Do not use if allergic to any of its ingredients.

Keep out of reach of children. If swallowed, get medical help or contact Poison Control immediately.

Do Not Use

If pregnant, breast feeding or intending to become pregnant.

Precautions

Stop use and consult a physician if pain persists beyond 3 days, a rash or irritation develops, or if condition worsens, or resolves and then returns.

Directions

Adults and Children over 12.Apply an adequate amount of gel to cover affected area. On day 1 apply 2 to 3 times within the first hour, and up to six times that day. On the following days, apply 3 to 4 times a day, as needed.

Inactive Ingredients

Filtrated deionized water, MethylSulfonylMethane (MSM), Acrylates/C-10-30, Alkyl Acrylate Crosspolymer, Polysorbate-20, Propylene Glycol (and) Dizolidinyl Urea (and) Iodopropynyl Butylcarbamate, Ammonium Hydroxide.

Other Information

Store between 68° and 74°F (20°-23°C) with closed cover. Do not apply with hot pack.

Questions or Comments

Email us at: info@lubracane.com